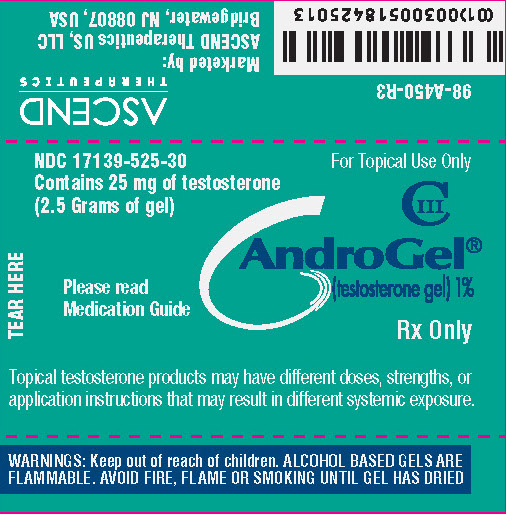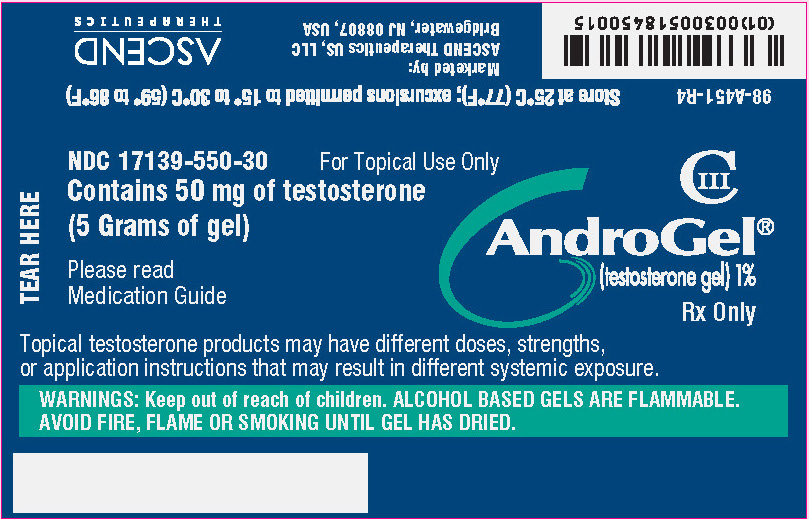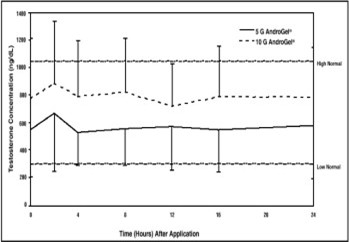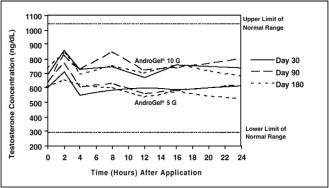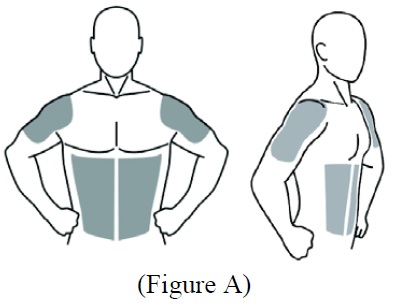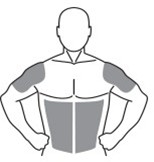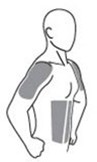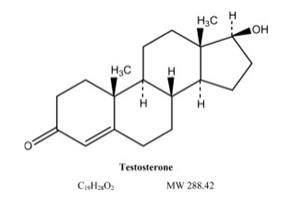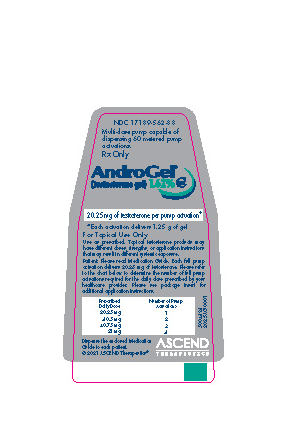 DRUG LABEL: AndroGel
NDC: 17139-501 | Form: GEL
Manufacturer: ASCEND Therapeutics U.S., LLC
Category: prescription | Type: HUMAN PRESCRIPTION DRUG LABEL
Date: 20250731
DEA Schedule: CIII

ACTIVE INGREDIENTS: TESTOSTERONE 10 mg/1 g
INACTIVE INGREDIENTS: ALCOHOL; ISOPROPYL MYRISTATE; WATER; SODIUM HYDROXIDE; CARBOMER HOMOPOLYMER TYPE C (ALLYL PENTAERYTHRITOL CROSSLINKED)

HIGHLIGHTS OF PRESCRIBING INFORMATION

These highlights do not include all the information needed to use ANDROGEL 1% safely and effectively. See full prescribing information for ANDROGEL 1%.
ANDROGEL® (testosterone gel) 1% for topical use CIII
Initial U.S. Approval: 1953

WARNING: SECONDARY EXPOSURE TO TESTOSTERONE

See full prescribing information for complete boxed warning.

- Virilization has been reported in children who were secondarily exposed to testosterone gel (5.1, 6.2).
- Children should avoid contact with unwashed or unclothed application sites in men using testosterone gel (2.2, 5.1).
- Healthcare providers should advise patients to strictly adhere to recommended instructions for use (2.2, 5.1, 17).

RECENT MAJOR CHANGES

Warnings and Precautions, Venous Thromboembolism (5.3) 07/2025
Warnings and Precautions, Blood Pressure Increases (5.5) 07/2025
Warnings and Precautions, Cardiovascular Risk (5.5) Removed 07/2025

1 INDICATIONS AND USAGE

AndroGel 1% is indicated for replacement therapy in males for conditions associated with a deficiency or absence of endogenous testosterone:

- Primary hypogonadism (congenital or acquired) (1)
- Hypogonadotropic hypogonadism (congenital or acquired) (1)

Limitations of use:

- Safety and efficacy of AndroGel 1% in men with “age-related hypogonadism” have not been established. (1)
- Safety and efficacy of AndroGel 1% in males less than 18 years old have not been established. (8.4)
- Topical testosterone products may have different doses, strengths, or application instructions that may result in different systemic exposure. (1, 12.3)

2 DOSAGE AND ADMINISTRATION

- Dosage and Administration for AndroGel 1% differs from AndroGel 1.62%. For dosage and administration of AndroGel 1.62% refer to its full prescribing information. (2)
- Prior to initiating AndroGel 1%, confirm the diagnosis of hypogonadism by ensuring that serum testosterone has been measured in the morning on at least two separate days and that these concentrations are below the normal range (2).
- Starting dose of AndroGel 1% is 50 mg of testosterone (4 pump actuations, two 25 mg packets or one 50 mg packet), applied once daily in the morning. (2.1)
- Apply to clean, dry, intact skin of shoulders and upper arms and/or abdomen. Do NOT apply AndroGel 1% to any other parts of the body including the genitals, chest, armpits (axillae), knees, or back. (2.2)
- Dose adjustment: AndroGel 1% can be dose adjusted using 50 mg, 75 mg, or 100 mg of testosterone on the basis of total serum testosterone concentration. The dose should be titrated based on the serum testosterone concentration. Additionally, serum testosterone concentration should be assessed periodically. (2.1)
- Patients should wash hands immediately with soap and water after applying AndroGel 1% and cover the application site(s) with clothing after the gel has dried. Wash the application site thoroughly with soap and water prior to any situation where skin-to-skin contact of the application site with another person is anticipated. (2.2)

3 DOSAGE FORMS AND STRENGTHS

AndroGel (testosterone gel) 1% for topical use is available as follows:

- Metered-dose pump that delivers 12.5 mg of testosterone per actuations (3)
- Packets containing 25 mg of testosterone. (3)
- Packets containing 50 mg of testosterone. (3)

4 CONTRAINDICATIONS

- Men with carcinoma of the breast or known or suspected prostate cancer (4, 5.4)
- Women who are pregnant. Testosterone may cause fetal harm (4, 8.1)

5 WARNINGS AND PRECAUTIONS

- Worsening of Benign Prostatic Hyperplasia (BPH) and Potential Risk of Prostate Cancer: Monitor patients with benign prostatic hyperplasia (BPH) for worsening of signs and symptoms of BPH. (5.4)
- Potential for Secondary Exposure to Testosterone: Avoid unintentional exposure of women or children to AndroGel 1%. Secondary exposure to testosterone can produce signs of virilization. AndroGel 1% should be discontinued until the cause of virilization is identified (5.1)
- Venous Thromboembolism (VTE): VTE including deep vein thrombosis (DVT) and pulmonary embolism (PE) have been reported in patients using testosterone products. Evaluate patients with signs or symptoms consistent with DVT or PE. (5.3)
- Blood Pressure Increases: AndroGel 1% can increase blood pressure, which can increase cardiovascular risk over time. Measure blood pressure periodically. Not recommended for use in men with uncontrolled hypertension (5.5)
- Potential for Adverse Effects on Spermatogenesis: Exogenous administration of androgens may lead to azoospermia (5.8)
- Edema: Edema with or without congestive heart failure (CHF) may be a complication in patients with preexisting cardiac, renal, or hepatic disease (5.10, 6.2)
- Sleep Apnea: Sleep apnea may occur in those with risk factors (5.12)
- Monitor serum testosterone, prostate specific antigen (PSA), hemoglobin, hematocrit, liver function tests and lipid concentrations periodically (5.4, 5.6, 5.9, 5.13)
- Flammability: AndroGel 1% is flammable until dry (5.16)

6 ADVERSE REACTIONS

Most common adverse reactions (incidence ≥ 5%) are acne, application site reaction, abnormal lab tests, and prostatic disorders. (6.1)

To report SUSPECTED ADVERSE REACTIONS, contact ASCEND Therapeutics US, LLC at 1-877-204-1013 or FDA at 1-800-FDA-1088 or www.fda.gov/medwatch.

7 DRUG INTERACTIONS

- Androgens may decrease blood glucose and therefore may decrease insulin requirements in diabetic patients. (7.2)
- Changes in anticoagulant activity may be seen with androgens. More frequent monitoring of INR and prothrombin time is recommended. (7.2)
- Use of testosterone with adrenocorticotrophic hormone (ACTH) or corticosteroids may result in increased fluid retention. Use with caution, particularly in patients with cardiac, renal, or hepatic disease. (7.3)

8 USE IN SPECIFIC POPULATIONS

There are insufficient long-term safety data in geriatric patients using AndroGel 1% to assess the potential risks of cardiovascular disease and prostate cancer. (8.5)

FULL PRESCRIBING INFORMATION

WARNING: SECONDARY EXPOSURE TO TESTOSTERONE

- Virilization has been reported in children who were secondarily exposed to testosterone gel [see Warnings and Precautions (5.1) and Adverse Reactions (6.2)].
- Children should avoid contact with unwashed or unclothed application sites in men using testosterone gel [see Dosage and Administration (2.2) and Warnings and Precautions (5.1)].
- Healthcare providers should advise patients to strictly adhere to recommended instructions for use [see Dosage and Administration (2.2), Warnings and Precautions (5.1) and Patient Counseling Information (17)].

1 INDICATIONS AND USAGE

AndroGel 1% is indicated for replacement therapy in adult males for conditions associated with a deficiency or absence of endogenous testosterone:

- Primary hypogonadism (congenital or acquired): testicular failure due to conditions such as cryptorchidism, bilateral torsion, orchitis, vanishing testis syndrome, orchiectomy, Klinefelter's syndrome, chemotherapy, or toxic damage from alcohol or heavy metals. These men usually have low serum testosterone concentrations and gonadotropins (follicle-stimulating hormone [FSH], luteinizing hormone [LH]) above the normal range.
- Hypogonadotropic hypogonadism (congenital or acquired): gonadotropin or luteinizing hormone-releasing hormone (LHRH) deficiency or pituitary-hypothalamic injury from tumors, trauma, or radiation. These men have low testosterone serum concentrations, but have gonadotropins in the normal or low range.

Limitations of use:

- Safety and efficacy of AndroGel 1% in men with “age-related hypogonadism” (also referred to as “late-onset hypogonadism”) have not been established.
- Safety and efficacy of AndroGel 1% in males less than 18 years old have not been established [see Use in Specific Populations (8.4)].
- Topical testosterone products may have different doses, strengths, or application instructions that may result in different systemic exposure (1, 12.3).

2 DOSAGE AND ADMINISTRATION

Dosage and Administration for AndroGel 1% differs from AndroGel 1.62%. For dosage and administration of AndroGel 1.62% refer to its full prescribing information. (2)

Prior to initiating AndroGel 1%, confirm the diagnosis of hypogonadism by ensuring that serum testosterone concentrations have been measured in the morning on at least two separate days and that these serum testosterone concentrations are below the normal range.

2.1 Dosing and Dose Adjustment

The recommended starting dose of AndroGel 1% is 50 mg of testosterone (4 pump actuations, two 25 mg packets or one 50 mg packet), applied topically once daily in the morning to the shoulders and upper arms and/or abdomen area (preferably at the same time every day).

Dose Adjustment

To ensure proper dosing, serum testosterone concentrations should be measured at intervals. If the serum testosterone concentration is below the normal range, the daily AndroGel 1% dose may be increased from 50 mg to 75 mg and from 75 mg to 100 mg for adult males as instructed by the physician. If the serum testosterone concentration exceeds the normal range, the daily AndroGel 1% dose may be decreased. If the serum testosterone concentration consistently exceeds the normal range at a daily dose of 50 mg, AndroGel 1% therapy should be discontinued. In addition, serum testosterone concentrations should be assessed periodically.

The application site and dose of AndroGel 1% are not substitutable with other topical testosterone products.

2.2 Administration Instructions

AndroGel 1% should be applied to clean, dry, healthy, intact skin of the right and left upper arms/shoulders and/or right and left abdomen. Area of application should be limited to the area that will be covered by the patient’s short sleeve T-shirt. Do not apply AndroGel 1% to any other part of the body including the genitals, chest, armpits (axillae), knees, or back. AndroGel 1% should be evenly distributed between the right and left upper arms/shoulders or both sides of the abdomen.

The prescribed daily dose of AndroGel 1% should be applied to the right and left upper arms/shoulders and/or right/left abdomen as shown in the shaded areas in the figures below.

After applying the gel, the application site should be allowed to dry prior to dressing. Hands should be washed thoroughly with soap and water after application. Avoid fire, flames or smoking until the gel has dried since alcohol-based products, including AndroGel 1%, are flammable.

The patient should be advised to avoid swimming or showering for at least 5 hours after the application of AndroGel 1%.

Multi-Dose Pump

To obtain a full first dose, it is necessary to prime the canister pump. To do so, with the canister in the upright position, slowly and fully depress the actuator three times. Safely discard the gel from the first three actuations. It is only necessary to prime the pump before the first dose. After the priming procedure, patients should completely depress the pump one time actuation for every 12.5 mg of testosterone required to achieve the daily prescribed dosage. The product should be delivered directly into the palm of the hand and then applied to the desired application sites. Alternatively, AndroGel 1% can be applied directly to the application sites. Table 1 provides dosing information for adult males.

Table 1: Dosing Information for AndroGel 1%
Amount of Testosterone | Number of Pump Actuations
50 mg | 4 (once daily)
75 mg | 6 (once daily)
100 mg | 8 (once daily)

Packets

The entire contents should be squeezed into the palm of the hand and immediately applied to the application sites. Alternately, patients may squeeze a portion of the gel from the packet into the palm of the hand and apply to application sites. Repeat until entire contents have been applied.

Strict adherence to the following precautions is advised in order to minimize the potential for secondary exposure to testosterone from AndroGel 1%-treated skin:

- Children and women should avoid contact with unwashed or unclothed application site(s) of men using AndroGel 1%.
- Patients should wash hands with soap and water immediately after application of AndroGel 1%.
- Patients should cover the application site(s) with clothing (e.g., a T-shirt) after the gel has dried.
- Prior to situation in which direct skin-to-skin contact is anticipated, patients should wash the application site thoroughly with soap and water to remove any testosterone residue.
- In the event that unwashed or unclothed skin to which AndroGel 1% has been applied comes in direct contact with the skin of another person, the general area of contact on the other person should be washed with soap and water as soon as possible.

3 DOSAGE FORMS AND STRENGTHS

AndroGel (testosterone gel) 1% for topical use only, is available as follows:

- A metered-dose pump. Each pump actuation delivers 12.5 mg of testosterone in 1.25g of gel.
- A unit dose packet containing 25 mg of testosterone provided in 2.5 g of gel.
- A unit dose packet containing 50 mg of testosterone provided in 5 g of gel.

4 CONTRAINDICATIONS

- AndroGel 1% is contraindicated in men with carcinoma of the breast or known or suspected carcinoma of the prostate [see Warnings and Precautions (5.4), Adverse Reactions (6.1), and Nonclinical Toxicology (13.1)].
- AndroGel 1% is contraindicated in women who are pregnant. AndroGel 1% can cause virilization of the female fetus when administered to a pregnant woman. Pregnant women need to be aware of the potential for transfer of testosterone from men treated with AndroGel 1%. If a pregnant woman is exposed to AndroGel 1%, she should be apprised of the potential hazard to the fetus [see Warnings and Precautions (5.1) and Use in Specific Populations (8.1)].

5 WARNINGS AND PRECAUTIONS

5.1 Potential for Secondary Exposure to Testosterone

Cases of secondary exposure resulting in virilization of children have been reported in postmarketing surveillance. Signs and symptoms have included enlargement of the penis or clitoris, development of pubic hair, increased erections and libido, aggressive behavior, and advanced bone age. In most cases, these signs and symptoms regressed with removal of the exposure to testosterone gel. In a few cases, however, enlarged genitalia did not fully return to age-appropriate normal size, and bone age remained modestly greater than chronological age. The risk of transfer was increased in some of these cases by not adhering to precautions for the appropriate use of the topical testosterone product. Children and women should avoid contact with unwashed or unclothed application sites in men using AndroGel 1% [see Dosage and Administration (2.2), Use in Specific Populations (8.1) and Clinical Pharmacology (12.3)].

Inappropriate changes in genital size or development of pubic hair or libido in children, or changes in body hair distribution, significant increase in acne, or other signs of virilization in adult women should be brought to the attention of a physician and the possibility of secondary exposure to testosterone gel should also be brought to the attention of a physician. Testosterone gel should be promptly discontinued until the cause of virilization has been identified.

5.2 Polycythemia

Increases in hematocrit, reflective of increases in red blood cell mass, may require lowering or discontinuation of testosterone. Check hematocrit prior to initiating treatment. It would also be appropriate to re-evaluate the hematocrit 3 to 6 months after starting treatment, and then annually. If hematocrit becomes elevated, stop therapy until hematocrit decreases to an acceptable concentration. An increase in red blood cell mass may increase the risk of thromboembolic events.

5.3 Venous Thromboembolism

There have been postmarketing reports of venous thromboembolic events (VTE), including deep vein thrombosis (DVT) and pulmonary embolism (PE), in patients using testosterone products such as AndroGel 1%.

In the Testosterone Replacement therapy for Assessment of long-term Vascular Events and efficacy ResponSE in hypogonadal men (TRAVERSE) Study, a randomized, double-blind, placebo-controlled, cardiovascular (CV) outcomes study, compared to placebo, AndroGel 1% was associated with a numerically higher incidence of VTE (1.7% vs 1.2%) which included DVT (0.6% vs 0.5%) and PE events (0.9% vs 0.5%) [see Adverse Reactions (6.1)].

Evaluate patients who report symptoms of pain, edema, warmth and erythema in the lower extremity for DVT and those who present with acute shortness of breath for PE. If a venous thromboembolic event is suspected, discontinue treatment with AndroGel 1% and initiate appropriate workup and management [see Adverse Reactions (6.2)].

5.4 Worsening of Benign Prostatic Hyperplasia (BPH) and Potential Risk of Prostate Cancer

- Patients with BPH treated with androgens are at an increased risk for worsening of signs and symptoms of BPH. Monitor patients with BPH for worsening signs and symptoms.
- Patients treated with androgens may be at increased risk for prostate cancer. Evaluate patients for prostate cancer prior to initiating and during treatment with androgens [see Contraindications (4), Adverse Reactions (6.1) and Nonclinical Toxicology (13.1)].

5.5 Blood Pressure Increases

AndroGel 1% can increase blood pressure. In an ambulatory blood pressure monitoring (ABPM) study, AndroGel 1.62% increased the mean systolic/diastolic blood pressure by 1.9/1.3 mm Hg from baseline after 16 weeks of treatment. In patients with hypertension on antihypertensive therapy, AndroGel 1.62% increased the mean systolic/diastolic BP by 3.0/2.2 mm Hg from baseline. Blood pressure increases can increase cardiovascular (CV) risk over time.

The CV risk associated with AndroGel 1.62% was evaluated in TRAVERSE, a randomized, double-blind, placebo-controlled, CV outcomes study in men with a history of CV disease or multiple CV risk factors. In TRAVERSE, mean systolic blood pressure in the group treated with AndroGel 1.62% was increased by 1.0 mm Hg from baseline to 36 months, whereas a mean decrease from baseline of 0.5 mm Hg was observed in the placebo group at this timepoint, for a mean between-group difference of 1.5 mm Hg. However, the incidences of major adverse cardiovascular events (MACE), including cardiovascular death, non-fatal myocardial infarction [MI] and non-fatal stroke, were similar between treatment groups (7% for AndroGel 1.62% vs 7.3% for placebo) [See Adverse Reactions (6.1)].

Monitor blood pressure periodically in men using AndroGel 1.62%, especially men with hypertension. AndroGel 1.62% is not recommended for use in patients with uncontrolled hypertension.

5.6 Abuse of Testosterone and Monitoring of Serum Testosterone Concentrations

Testosterone has been subject to abuse, typically at doses higher than recommended for the approved indication and in combination with other anabolic androgenic steroids. Anabolic androgenic steroid abuse can lead to serious cardiovascular and psychiatric adverse reactions [see Drug Abuse and Dependence (9)].

If testosterone abuse is suspected, check serum testosterone concentrations to ensure they are within therapeutic range. However, testosterone levels may be in the normal or subnormal range in men abusing synthetic testosterone derivatives. Counsel patients concerning the serious adverse reactions associated with abuse of testosterone and anabolic androgenic steroids. Conversely, consider the possibility of testosterone and anabolic androgenic steroid abuse in suspected patients who present with serious cardiovascular or psychiatric adverse events.

5.7 Not for Use in Women

Due to the lack of controlled evaluations in women and potential virilizing effects, AndroGel 1% is not indicated for use in women [see Contraindications (4) and Use in Specific Populations (8.1, 8.2)].

5.8 Potential for Adverse Effects on Spermatogenesis

With large doses of exogenous androgens, including AndroGel 1%, spermatogenesis may be suppressed through feedback inhibition of pituitary follicle-stimulating hormone (FSH) which could possibly lead to adverse effects on semen parameters including sperm count.

5.9 Hepatic Adverse Effects

Prolonged use of high doses of orally active 17-alpha-alkyl androgens (e.g., methyltestosterone) has been associated with serious hepatic adverse effects (peliosis hepatis, hepatic neoplasms, cholestatic hepatitis, and jaundice). Peliosis hepatis can be a life-threatening or fatal complication. Long-term therapy with intramuscular testosterone enanthate has produced multiple hepatic adenomas. AndroGel 1% is not known to cause these adverse effects.

5.10 Edema

Androgens, including AndroGel 1%, may promote retention of sodium and water. Edema, with or without congestive heart failure, may be a serious complication in patients with preexisting cardiac, renal, or hepatic disease [see Adverse Reactions (6.2)].

5.11 Gynecomastia

Gynecomastia may develop and persist in patients being treated with androgens, including AndroGel 1%, for hypogonadism.

5.12 Sleep Apnea

The treatment of hypogonadal men with testosterone may potentiate sleep apnea in some patients, especially those with risk factors such as obesity or chronic lung diseases [see Adverse Reactions (6.2)].

5.13 Lipid Changes

Changes in serum lipid profile may require dose adjustment or discontinuation of testosterone therapy, such as AndroGel 1%. Monitor the lipid profile periodically, particularly after starting testosterone therapy.

5.14 Hypercalcemia

Androgens, including AndroGel 1%, should be used with caution in cancer patients at risk of hypercalcemia (and associated hypercalciuria). Regular monitoring of serum calcium concentrations is recommended in these patients.

5.15 Decreased Thyroxine-binding Globulin

Androgens, including AndroGel 1%, may decrease concentrations of thyroxin-binding globulins, resulting in decreased total T4 serum concentrations and increased resin uptake of T3 and T4. Free thyroid hormone concentrations remain unchanged, however, and there is no clinical evidence of thyroid dysfunction.

5.16 Flammability

Alcohol based products, including AndroGel 1%, are flammable; therefore, patients should be advised to avoid fire, flame or smoking until the AndroGel 1% has dried.

6 ADVERSE REACTIONS

6.1 Clinical Trial Experience

Because clinical trials are conducted under widely varying conditions, adverse reaction rates observed in the clinical trials of a drug cannot be directly compared to rates in the clinical trials of another drug and may not reflect the rates observed in practice.

Clinical Trials in Hypogonadal Men

Table 2 shows the incidence of all adverse events judged by the investigator to be at least possibly related to treatment with AndroGel 1% and reported by >1% of patients in a 180 Day, Phase 3 study.

Table 2: Adverse Events Possibly, Probably or Definitely Related to Use of AndroGel 1% in the 180-Day Controlled Clinical Trial
Adverse Event | Dose of AndroGel 1%
Adverse Event | 50 mg | 75 mg | 100 mg
 | N = 77 | N = 40 | N = 78
Acne | 1% | 3% | 8%
Alopecia | 1% | 0% | 1%
Application Site Reaction | 5% | 3% | 4%
Asthenia | 0% | 3% | 1%
Depression | 1% | 0% | 1%
Emotional Lability | 0% | 3% | 3%
Gynecomastia | 1% | 0% | 3%
Headache | 4% | 3% | 0%
Hypertension | 3% | 0% | 3%
Lab Test Abnormal* | 6% | 5% | 3%
Libido Decreased | 0% | 3% | 1%
Nervousness | 0% | 3% | 1%
Pain Breast | 1% | 3% | 1%
Prostate Disorder** | 3% | 3% | 5%
Testis Disorder*** | 3% | 0% | 0%
*Lab test abnormal occurred in nine patients with one or more of the following events reported: elevated hemoglobin or hematocrit, hyperlipidemia, elevated triglycerides, hypokalemia, decreased HDL, elevated glucose, elevated creatinine, elevated total bilirubin.
**Prostate disorders included five patients with enlarged prostate, one with BPH, and one with elevated PSA results.
***Testis disorders were reported in two patients: one with left varicocele and one with slight sensitivity of left testis.

Other less common adverse reactions, reported in fewer than 1% of patients included: amnesia, anxiety, discolored hair, dizziness, dry skin, hirsutism, hostility, impaired urination, paresthesia, penis disorder, peripheral edema, sweating, and vasodilation.

In this 180-day clinical trial, skin reactions at the site of application were reported with AndroGel 1%, but none was severe enough to require treatment or discontinuation of drug.

Six patients (4%) in this trial had adverse events that led to discontinuation of AndroGel 1%. These events included: cerebral hemorrhage, convulsion (neither of which were considered related to AndroGel 1% administration), depression, sadness, memory loss, elevated prostate specific antigen, and hypertension. No AndroGel 1% patient discontinued due to skin reactions.

In a separate uncontrolled pharmacokinetic study of 10 patients, two had adverse events associated with AndroGel 1%; these were asthenia and depression in one patient and increased libido and hyperkinesia in the other.

In a 3-year, flexible dose, extension study, the incidence of all adverse events judged by the investigator to be at least possibly related to treatment with AndroGel 1% and reported by > 1% of patients is shown in Table 3.

Table 3: Adverse Events Possibly, Probably or Definitely Related to Use of Testosterone Gel 1% in the 3 Year, Flexible Dose, Extension Study
 | Percent of Subjects
Adverse Event | (N = 162)
Lab Test Abnormal+ | 9.3
Skin dry | 1.9
Application Site Reaction | 5.6
Acne | 3.1
Pruritus | 1.9
Enlarged Prostate | 11.7
Carcinoma of Prostate | 1.2
Urinary Symptoms* | 3.7
Testis Disorder** | 1.9
Gynecomastia | 2.5
Anemia | 2.5
+Lab test abnormal occurred in 15 patients with one or more of the following events reported: elevated AST, elevated ALT, elevated testosterone, elevated hemoglobin or hematocrit, elevated cholesterol, elevated cholesterol/LDL ratio, elevated triglycerides, elevated HDL, elevated serum creatinine.
*Urinary symptoms included nocturia, urinary hesitancy, urinary incontinence, urinary retention, urinary urgency and weak urinary stream.
**Testis disorders included three patients. There were two with a non-palpable testis and one with slight right testicular tenderness.

Two patients reported serious adverse events considered possibly related to treatment: deep vein thrombosis (DVT) and prostate disorder requiring a transurethral resection of the prostate (TURP).

Discontinuation for adverse events in this study included: two patients with application site reactions, one with kidney failure, and five with prostate disorders (including increase in serum PSA in 4 patients, and increase in PSA with prostate enlargement in a fifth patient).

Increases in Serum PSA Observed in Clinical Trials of Hypogonadal Men

During the initial 6-month study, the mean change in PSA values had a statistically significant increase of 0.26 ng/mL. Serum PSA was measured every 6 months thereafter in the 162 hypogonadal men on AndroGel 1% in the 3-year extension study. There was no additional statistically significant increase observed in mean PSA from 6 months through 36 months. However, there were increases in serum PSA observed in approximately 18% of individual patients. The overall mean change from baseline in serum PSA values for the entire group from month 6 to 36 was 0.11 ng/mL.

Twenty-nine patients (18%) met the per-protocol criterion for increase in serum PSA, defined as >2X the baseline or any single serum PSA >6 ng/mL. Most of these (25/29) met this criterion by at least doubling of their PSA from baseline. In most cases where PSA at least doubled (22/25), the maximum serum PSA value was still <2 ng/mL. The first occurrence of a pre-specified, post- baseline increase in serum PSA was seen at or prior to Month 12 in most of the patients who met this criterion (23 of 29; 79%).

Four patients met this criterion by having a serum PSA >6 ng/mL and in these, maximum serum PSA values were 6.2 ng/mL, 6.6 ng/mL, 6.7 ng/mL, and 10.7 ng/mL. In two of these patients, prostate cancer was detected on biopsy. The first patient’s PSA levels were 4.7 ng/mL and 6.2 ng/mL at baseline and at Month 6/Final, respectively. The second patient’s PSA levels were 4.2 ng/mL, 5.2 ng/mL, 5.8 ng/mL, and 6.6 ng/mL at baseline, Month 6, Month 12, and Final, respectively.

Blood Pressure Increases

In a 4-month clinical study, 24-hour ambulatory blood pressure monitoring (ABPM) was conducted on 246 patients. ABPM was conducted at baseline and at Week 16 of AndroGel 1.62% therapy. A total of 169 patients had acceptable ABPM recordings at both baseline and Week 16 and also were at least 85% compliant with study drug. In that group, the mean change in 24-hour systolic blood pressure (BP) and diastolic BP from baseline to end-of-treatment at Week 16 (n=169) was 1.9 mm Hg (95% CI 0.6, 3.1) and 1.3 mm Hg (95% CI 0.5, 2.1), respectively. In patients with a history of hypertension who were being treated with antihypertensive therapy, the mean ABPM systolic and diastolic BP increased by 3.0 mm Hg [95% CI 0.8, 5.2] and 2.2 mm Hg [95% CI 0.8, 3.5], respectively [n=72]). In patients with no history of hypertension at baseline, the mean systolic and diastolic blood pressure increased by 1.2 mm Hg [95% CI -0.2, 2.7] and 0.9 mm Hg [95% CI -0.1, 1.8], respectively [n=91]).

Four patients (2.8%) on AndroGel 1.62%, all of whom were receiving antihypertensive medications at baseline, either started new antihypertensive medications (n=2) or had their antihypertensive regimen adjusted during the ABPM study.

Of the 246 patients who used AndroGel during the study, 10 patients (4.1%) were reported to have either an adverse reaction of hypertension (5 patients, 2.0%) or increased blood pressure (5 patients, 2.0%).

Cardiovascular Outcomes

TRAVERSE was a randomized, double-blind, cardiovascular outcomes study to assess the CV safety of AndroGel 1.62% compared to placebo in 5198 hypogonadal men aged 45 to 80 years with a history of CV disease or with multiple CV risk factors. The primary outcome was the incidence of the composite endpoint of major adverse cardiovascular events (MACE), consisting of CV death, non-fatal myocardial infarction (MI), and non-fatal stroke.

The mean duration of therapy was approximately 22 months. The mean duration of follow-up was 33 months. Approximately 61% of all patients discontinued AndroGel 1.62% or placebo therapy. The mean (±SD) daily dose of testosterone was 65±22 mg.

The mean patient age (±SD) was 63.3 (7.9) years, with 2452 patients aged 65 years or more (47%); 2847 (about 55%) patients had pre-existing cardiovascular disease, whereas 2357 patients (about 45%) had an elevated cardiovascular risk at baseline, and mean BMI was 35kg/m2. Approximately 80% of patients were White, 17% were Black, and 3% were of other races or ethnic groups. Approximately 69%, 84%, and 93% had diabetes mellitus, hyperlipidemia, and hypertension, respectively.

The mean serum testosterone concentration at baseline in patients receiving AndroGel 1.62% was 220.4 ng/dL (n= 2596). The mean serum testosterone concentrations at 12 months, 24 months, 36 months, and 48 months in patients receiving AndroGel 1.62% were 440.5 ng/dL (n=1683), 420.9 ng/dl (n=1125), 428.7 ng/dL (n=731), and 365.2 ng/dL (n=220), respectively.

For patients treated with AndroGel 1.62%, the incidence of MACE was 7.0% (n=182 events) and for those receiving placebo, the incidence of MACE was 7.3% (n=190 events). The study demonstrated non-inferiority of AndroGel 1.62% versus placebo because the upper bound of 95% CI was less than the pre-specified risk margin, of 1.5 for MACE (Hazard Ratio 0.96 [95% CI: 0.78, 1.17]).

Additional Adverse Reactions Reported in TRAVERSE

Additional adverse reactions reported in TRAVERSE at an incidence rate >2% in either treatment group and greater in AndroGel 1.62% versus placebo included: nonfatal arrythmias warranting intervention (5.2% vs 3.3%), atrial fibrillation (3.5% vs 2.4%), acute kidney injury (2.3% vs 1.5%) and bone fracture (3.5% vs 2.5%). For the adverse reaction of bone fracture, each event was adjudicated by clinical review.

6.2 Postmarketing Experience

The following adverse reactions have been identified during post approval use of AndroGel 1%. Because the reactions are reported voluntarily from a population of uncertain size, it is not always possible to reliably estimate their frequency or establish a causal relationship to drug exposure (Table 4).

Table 4: Adverse Drug Reactions from Postmarketing Experience of Testosterone Gel 1% by MedDRA System Organ Class
Blood and the lymphatic system disorders: | Elevated Hgb, Hct (polycythemia)
Cardiovascular disorders: | Myocardial infarction, stroke
Endocrine disorders: | Hirsutism
Gastrointestinal disorders: | Nausea
General disorders and administration site reactions: | Asthenia, edema, malaise
Genitourinary disorders: | Impaired urination
Hepatobiliary disorders: | Abnormal liver function tests (e.g. transaminases, elevated GGTP, bilirubin)
Investigations: | Elevated PSA, electrolyte changes (nitrogen, calcium, potassium, phosphorus, sodium), changes in serum lipids (hyperlipidemia, elevated triglycerides, decreased HDL), impaired glucose tolerance, fluctuating testosterone concentrations, weight increase
Neoplasms benign, malignant and unspecified (cysts and polyps): | Prostate cancer
Nervous system: | Headache, dizziness, sleep apnea, insomnia
Psychiatric disorders: | Depression, emotional lability, decreased libido, nervousness, hostility, amnesia, anxiety
Reproductive system and breast disorders: | Gynecomastia, mastodynia, prostatic enlargement, testicular atrophy, oligospermia, priapism (frequent or prolonged erections)
Respiratory disorders: | Dyspnea
Skin and subcutaneous tissue disorders: | Acne, alopecia, application site reaction (pruritus, dry skin, erythema, rash, discolored hair, paresthesia), sweating
Vascular disorders: | Hypertension, vasodilation (hot flushes), venous thromboembolism

Secondary Exposure to Testosterone in Children

Cases of secondary exposure to testosterone resulting in virilization of children have been reported in postmarket surveillance. Signs and symptoms of these reported cases have included enlargement of the clitoris (with surgical intervention) or the penis, development of pubic hair, increased erections and libido, aggressive behavior, and advanced bone age. In most cases with a reported outcome, these signs and symptoms were reported to have regressed with removal of the testosterone gel exposure. In a few cases, however, enlarged genitalia did not fully return to age-appropriate normal size, and bone age remained modestly greater than chronological age. In some of the cases, direct contact with the sites of application on the skin of men using testosterone gel was reported. In at least one reported case, the reporter considered the possibility of secondary exposure from items such as the testosterone gel user's shirts and/or other fabric, such as towels and sheets [see Warnings and Precautions (5.1)].

7 DRUG INTERACTIONS

7.1 Insulin

Changes in insulin sensitivity or glycemic control may occur in patients treated with androgens. In diabetic patients, the metabolic effects of androgens may decrease blood glucose and, therefore, may decrease insulin requirements.

7.2 Oral Anticoagulants

Changes in anticoagulant activity may be seen with androgens, therefore more frequent monitoring of international normalized ratio (INR) and prothrombin time are recommended in patients taking anticoagulants, especially at the initiation and termination of androgen therapy.

7.3 Corticosteroids

The concurrent use of testosterone with adrenocorticotropic hormone (ACTH) or corticosteroids may result in increased fluid retention and requires careful monitoring particularly in patients with cardiac, renal or hepatic disease.

8 USE IN SPECIFIC POPULATIONS

8.1 Pregnancy

Risk Summary

AndroGel 1% is contraindicated in pregnant women. Testosterone is teratogenic and may cause fetal harm when administered to a pregnant woman based on data from animal studies and its mechanism of action [see Contraindications (4) and Clinical Pharmacology (12.1)]. Exposure of a female fetus to androgens may result in varying degrees of virilization. In animal developmental studies, exposure to testosterone in utero resulted in hormonal and behavioral changes in offspring and structural impairments of reproductive tissues in female and male offspring. These studies did not meet current standards for nonclinical development toxicity studies.

Data

Animal Data

In developmental studies conducted in rats, rabbits, pigs, sheep and rhesus monkeys, pregnant animals received intramuscular injection of testosterone during the period of organogenesis. Testosterone treatment at doses that were comparable to those used for testosterone replacement therapy resulted in structural impairments in both female and male offspring. Structural impairments observed in females included increased ano-genital distance, phallus development, empty scrotum, no external vagina, intrauterine growth retardation, reduced ovarian reserve, and increased ovarian follicular recruitment. Structural impairments seen in male offspring included increased testicular weight, larger seminal tubular lumen diameter, and higher frequency of occluded tubule lumen. Increased pituitary weight was seen in both sexes.

Testosterone exposure in utero also resulted in hormonal and behavioral changes in offspring. Hypertension was observed in pregnant female rats and their offspring exposed to doses approximately twice those used for testosterone replacement therapy.

8.2 Lactation

Risk Summary

AndroGel 1% is not indicated for use in women.

8.3 Females and Males of Reproductive Potential

Infertility

Testis disorder, testicular atrophy, and oligospermia have been identified during use of AndroGel 1% [see Adverse Reactions (6.1, 6.2)].

During treatment with large doses of exogenous androgens, including AndroGel 1%, spermatogenesis may be suppressed through feedback inhibition of the hypothalamic-pituitary-testicular axis [see Warnings and Precautions (5.8)]. Reduced fertility is observed in some men taking testosterone replacement therapy. Testicular atrophy, subfertility, and infertility have also been reported in men who abuse anabolic androgenic steroids [see Drug Abuse and Dependence (9.2)]. With either type of use, the impact on fertility may be irreversible.

8.4 Pediatric Use

The safety and effectiveness of AndroGel 1% in pediatric patients less than 18 years old has not been established. Improper use may result in acceleration of bone age and premature closure of epiphyses.

8.5 Geriatric Use

There have not been sufficient numbers of geriatric patients involved in controlled clinical studies utilizing AndroGel 1% to determine whether efficacy in those over 65 years of age differs from younger subjects. Additionally, there is insufficient long-term safety data in geriatric patients to assess the potential risks of cardiovascular disease and prostate cancer.

Geriatric patients treated with androgens may also be at risk for worsening of signs and symptoms of BPH.

8.6 Renal Impairment

No studies were conducted involving patients with renal impairment.

8.7 Hepatic Impairment

No studies were conducted in patients with hepatic impairment.

9 DRUG ABUSE AND DEPENDENCE

9.1 Controlled Substance

AndroGel 1% contains testosterone, a Schedule III controlled substance in the Controlled Substances Act.

9.2 Abuse

Drug abuse is intentional non-therapeutic use of a drug, even once, for its rewarding psychological and physiological effects. Abuse and misuse of testosterone are seen in male and female adults and adolescents. Testosterone, often in combination with other anabolic androgenic steroids (AAS), and not obtained by prescription through a pharmacy, may be abused by athletes and bodybuilders. There have been reports of misuse by men taking higher doses of legally obtained testosterone than prescribed and continuing testosterone despite adverse events or against medical advice.

Abuse-Related Adverse Reactions

Serious adverse reactions have been reported in individuals who abuse anabolic androgenic steroids and include cardiac arrest, myocardial infarction, hypertrophic cardiomyopathy, congestive heart failure, cerebrovascular accident, hepatotoxicity, and serious psychiatric manifestations, including major depression, mania, paranoia, psychosis, delusions, hallucinations, hostility and aggression.

The following adverse reactions have also been reported in men: transient ischemic attacks, convulsions, hypomania, irritability, dyslipidemias, testicular atrophy, subfertility, and infertility.

The following additional adverse reactions have been reported in women: hirsutism, virilization, deepening of voice, clitoral enlargement, breast atrophy, male-pattern baldness, and menstrual irregularities.

The following adverse reactions have been reported in male and female adolescents: premature closure of bony epiphyses with termination of growth, and precocious puberty.

Because these reactions are reported voluntarily from a population of uncertain size and may include abuse of other agents, it is not always possible to reliably estimate their frequency or establish a causal relationship to drug exposure.

9.3 Dependence

Behaviors Associated with Addiction

Continued abuse of testosterone and other anabolic steroids, leading to addiction is characterized by the following behaviors:

- Taking greater dosages than prescribed
- Continued drug use despite medical and social problems due to drug use
- Spending significant time to obtain the drug when supplies of the drug are interrupted
- Giving a higher priority to drug use than other obligations
- Having difficulty in discontinuing the drug despite desires and attempts to do so
- Experiencing withdrawal symptoms upon abrupt discontinuation of use

Physical dependence is characterized by withdrawal symptoms after abrupt drug discontinuation or a significant dose reduction of a drug. Individuals taking supratherapeutic doses of testosterone may experience withdrawal symptoms lasting for weeks or months which include depressed mood, major depression, fatigue, craving, restlessness, irritability, anorexia, insomnia, decreased libido and hypogonadotropic hypogonadism.

Drug dependence in individuals using approved doses of testosterone for approved indications has not been documented.

10 OVERDOSAGE

There is one report of acute overdosage with use of an approved injectable testosterone product: this subject had serum testosterone concentrations of up to 11,400 ng/dL with a cerebrovascular accident.

Treatment of overdosage would consist of discontinuation of AndroGel 1%, washing the application site with soap and water, and appropriate symptomatic and supportive care.

11 DESCRIPTION

AndroGel 1% for topical use is a clear, colorless gel containing testosterone. Testosterone is an androgen. AndroGel 1% is available in a metered-dose pump or unit dose packets.

The active pharmacologic ingredient in AndroGel 1% is testosterone, an androgen. Testosterone USP is a white to practically white crystalline powder chemically described as 17-beta hydroxyandrost-4-en-3-one. The structural formula is:

Pharmacologically inactive ingredients in AndroGel 1% are carbomer 980, ethanol 67.0%, isopropyl myristate, purified water, and sodium hydroxide. These ingredients are not pharmacologically active.

12 CLINICAL PHARMACOLOGY

12.1 Mechanism of Action

Endogenous androgens, including testosterone and dihydrotestosterone (DHT), are responsible for the normal growth and development of the male sex organs and for maintenance of secondary sex characteristics. These effects include the growth and maturation of prostate, seminal vesicles, penis and scrotum; the development of male hair distribution, such as facial, pubic, chest and axillary hair; laryngeal enlargement; vocal chord thickening; and alterations in body musculature and fat distribution. Testosterone and DHT are necessary for the normal development of secondary sex characteristics.

Male hypogonadism, a clinical syndrome resulting from insufficient secretion of testosterone, has two main etiologies. Primary hypogonadism is caused by defects of the gonads, such as Klinefelter's syndrome or Leydig cell aplasia, whereas secondary hypogonadism is the failure of the hypothalamus (or pituitary) to produce sufficient gonadotropins (FSH, LH).

12.2 Pharmacodynamics

No specific pharmacodynamic studies were conducted using AndroGel 1%.

12.3 Pharmacokinetics

Absorption

AndroGel 1% delivers physiologic amounts of testosterone, producing circulating testosterone concentrations that approximate normal concentrations (298 - 1043 ng/dL) seen in healthy men. AndroGel 1% provides continuous topical delivery of testosterone for 24 hours following a single application to intact, clean, dry skin of the shoulders, upper arms and/or abdomen.

AndroGel 1% is a hydroalcoholic formulation that dries quickly when applied to the skin surface. The skin serves as a reservoir for the sustained release of testosterone into the systemic circulation. Approximately 10% of the testosterone dose applied on the skin surface from AndroGel is absorbed into systemic circulation. In a study with AndroGel 1% 100 mg, all patients showed an increase in serum testosterone within 30 minutes, and eight of nine patients had a serum testosterone concentration within normal range by 4 hours after the initial application. Absorption of testosterone into the blood continues for the entire 24-hour dosing interval. Serum concentrations approximate the steady-state concentration by the end of the first 24 hours and are at steady state by the second or third day of dosing.

With single daily applications of AndroGel 1%, follow-up measurements 30, 90 and 180 days after starting treatment have confirmed that serum testosterone concentrations are generally maintained within the eugonadal range. Figure 1 summarizes the 24-hour pharmacokinetic profiles of testosterone for hypogonadal men (less than 300 ng/dL) maintained on AndroGel 1% 50 mg or 100 mg for 30 days. The average (± SD) daily testosterone concentration produced by AndroGel 1% 100 mg on Day 30 was 792 (± 294) ng/dL and by AndroGel 1% 50 mg 566 (±262) ng/dL.

Figure 1: Mean (± SD) Steady-State Serum Testosterone Concentrations on Day 30 in Patients Applying AndroGel 1% Once Daily

Distribution

Circulating testosterone is primarily bound in the serum to sex hormone-binding globulin (SHBG) and albumin. Approximately 40% of testosterone in plasma is bound to SHBG, 2% remains unbound (free) and the rest is bound to albumin and other proteins.

Metabolism

Testosterone is metabolized to various 17-keto steroids through two different pathways. The major active metabolites of testosterone are estradiol and dihydrotestosterone (DHT).

DHT concentrations increased in parallel with testosterone concentrations during AndroGel 1% treatment. The mean steady-state DHT/T ratio during 180 days of AndroGel treatment ranged from 0.23 to 0.29 (50 mg of AndroGel 1%/day) and from 0.27 to 0.33 (100 mg of AndroGel 1%/day).

Excretion

There is considerable variation in the half-life of testosterone concentration as reported in the literature, ranging from 10 to 100 minutes. About 90% of a dose of testosterone given intramuscularly is excreted in the urine as glucuronic and sulfuric acid conjugates of testosterone and its metabolites. About 6% of a dose is excreted in the feces, mostly in the unconjugated form. Inactivation of testosterone occurs primarily in the liver.

When AndroGel 1% treatment is discontinued after achieving steady state, serum testosterone concentrations remain in the normal range for 24 to 48 hours but return to their pretreatment concentrations by the fifth day after the last application.

Testosterone Transfer from Male Patients to Female Partners

The potential for dermal testosterone transfer following AndroGel 1% use was evaluated in a clinical study between males dosed with AndroGel 1% and their untreated female partners. Two (2) to 12 hours after application of 100 mg of testosterone administered as AndroGel 1% by the male subjects, the couples (N = 38 couples) engaged in daily, 15-minute sessions of vigorous skin-to-skin contact so that the female partners gained maximum exposure to the AndroGel 1% application sites. Under these study conditions, all unprotected female partners had a serum testosterone concentration >2 times the baseline value at some time during the study. When a shirt covered the application site(s), the transfer of testosterone from the males to the female partners was completely prevented.

13 NONCLINICAL TOXICOLOGY

13.1 Carcinogenesis, Mutagenesis, Impairment of Fertility

Carcinogenesis

Testosterone has been tested by subcutaneous injection and implantation in mice and rats. In mice, the implant induced cervical-uterine tumors which metastasized in some cases. There is suggestive evidence that injection of testosterone into some strains of female mice increases their susceptibility to hepatoma. Testosterone is also known to increase the number of tumors and decrease the degree of differentiation of chemically induced carcinomas of the liver in rats.

Mutagenesis

Testosterone was negative in the in vitro Ames and in the in vivo mouse micronucleus assays.

Impairment of Fertility

The administration of exogenous testosterone has been reported to suppress spermatogenesis in rats, dogs, and non-human primates, which was reversible on cessation of the treatment.

14 CLINICAL STUDIES

14.1 Clinical Trials in Hypogonadal Males

AndroGel 1% was evaluated in a multi-center, randomized, parallel-group, active-controlled, 180-day trial in 227 hypogonadal men. The study was conducted in 2 phases. During the Initial Treatment Period (Days 1-90), 73 patients were randomized to AndroGel 1% 50 mg daily, 78 patients to AndroGel 1% 100 mg daily, and 76 patients to a non-scrotal testosterone transdermal system. The study was double-blind for dose of AndroGel 1% but open-label for active control. Patients who were originally randomized to AndroGel 1% and who had single-sample serum testosterone concentrations above or below the normal range on Day 60 were titrated to 75 mg daily on Day 91. During the Extended Treatment Period (Days 91-180), 51 patients continued on AndroGel 1% 50 mg daily, 52 patients continued on AndroGel 1% 100 mg daily, 41 patients continued on a non-scrotal testosterone transdermal system (5 mg daily), and 40 patients received AndroGel 1% 75 mg daily. Upon completion of the initial study, 163 enrolled and 162 patients received treatment in an open-label extension study of AndroGel 1% for an additional period of up to 3 years.

Mean peak, trough and average serum testosterone concentrations within the normal range (298- 1043 ng/dL) were achieved on the first day of treatment with doses of 50 mg and 100 mg of AndroGel 1%. In patients continuing on AndroGel 1% 50 mg and 100 mg, these mean testosterone concentrations were maintained within the normal range for the 180-day duration of the original study. Figure 2 summarizes the 24-hour pharmacokinetic profiles of testosterone administered as AndroGel 1% for 30, 90 and 180 days. Testosterone concentrations were maintained as long as the patient continued to properly apply the prescribed AndroGel 1% treatment.

Figure 2: Mean Steady-State Testosterone Concentrations in Patients with Once-Daily AndroGel 1% Therapy

Table 5 summarizes the mean testosterone concentrations on Treatment Day 180 for patients receiving 50 mg, 75 mg, or 100 mg of AndroGel 1%. The 75 mg dose produced mean concentrations intermediate to those produced by 50 mg and 100 mg of AndroGel 1%.

Table 5: Mean (± SD) Steady-State Serum Testosterone Concentrations During Therapy (Day 180)
 | 50 mg | 75 mg | 100 mg
 | N = 44 | N = 37 | N = 48
Cavg | 555 ± 225 | 601 ± 309 | 713 ± 209
Cmax | 830 ± 347 | 901 ± 471 | 1083 ± 434
Cmin | 371 ± 165 | 406 ± 220 | 485 ± 156

Of 129 hypogonadal men who were appropriately titrated with AndroGel 1% and who had sufficient data for analysis, 87% achieved an average serum testosterone concentration within the normal range on Treatment Day 180.

In patients treated with AndroGel 1%, there were no observed differences in the average daily serum testosterone concentrations at steady-state based on age, cause of hypogonadism, or body mass index.

DHT concentrations increased in parallel with testosterone concentrations at AndroGel 1% doses of 50 mg/day and 100 mg/day, but the DHT/T ratio stayed within the normal range, indicating enhanced availability of the major physiologically active androgen. Serum estradiol (E2) concentrations increased significantly within 30 days of starting treatment with AndroGel 1% 50 or 100 mg/day and remained elevated throughout the treatment period but remained within the normal range for eugonadal men. Serum levels of SHBG decreased very slightly (1 to 11%) during AndroGel 1% treatment. In men with hypergonadotropic hypogonadism, serum levels of LH and FSH fell in a dose- and time-dependent manner during treatment with AndroGel 1%.

14.2 Phototoxicity in Humans

The phototoxic potential of AndroGel 1% was evaluated in a double-blind, single-dose study in 27 subjects with photosensitive skin types. The Minimal Erythema Dose (MED) of ultraviolet radiation was determined for each subject. A single 24 (+1) hour application of duplicate patches containing test articles (placebo gel, testosterone gel, or saline) was made to naive skin sites on Day 1. On Day 2, each subject received five exposure times of ultraviolet radiation, each exposure being 25% greater than the previous one. Skin evaluations were made on Days 2 to 5. Exposure of test and control article application sites to ultraviolet light did not produce increased inflammation relative to non-irradiated sites, indicating no phototoxic effect.

16 HOW SUPPLIED/STORAGE AND HANDLING

AndroGel 1% is supplied in non-aerosol, metered-dose pumps that deliver 12.5 mg of testosterone per complete pump actuation. The pumps are composed of plastic and stainless steel and an LDPE/aluminum foil inner liner encased in rigid plastic with a polypropylene cap. Each 88 g metered-dose pump is capable of dispensing 75 g of gel or 60-metered pump actuations; each pump actuation dispenses 1.25 g of gel.

AndroGel 1% is supplied in unit-dose aluminum foil packets in cartons of 30. Each packet of 2.5 g or 5 g gel contains 25 mg or 50 mg testosterone, respectively.

NDC Number | Package Size
17139-501-02 | 2 x 75 g pump (each pump dispenses 60 metered pump actuations with each pump actuation containing 12.5 mg of testosterone in 1.25 g of gel)
17139-525-30 | 30 packets (a unit dose packet containing 25 mg of testosterone provided in 2.5 g of gel)
17139-550-30 | 30 packets (each unit dose packet contains 20.25 mg of testosterone provided in 1.25 g of gel)

Storage

Store at 25°C (77°F); excursions permitted to 15°C to 30°C (59° to 86°F) [see USP Controlled Room Temperature].

Disposal

Used AndroGel 1% pumps or used AndroGel 1% packets should be discarded in household trash in a manner that prevents accidental application or ingestion by children or pets.

17 PATIENT COUNSELING INFORMATION

Advise the patient to read the FDA-approved patient labeling (Medication Guide).

Patients should be informed of the following:

17.1 Use in Men with Known or Suspected Prostate or Breast Cancer

Men with known or suspected prostate or breast cancer should not use AndroGel 1% [see Contraindications (4) and Warnings and Precautions (5.4)].

17.2 Potential for Secondary Exposure to Testosterone and Steps to Prevent Secondary Exposure

Secondary exposure to testosterone in children and women can occur with the use of testosterone gel in men [see Warnings and Precautions (5.1)]. Cases of secondary exposure to testosterone have been reported in children.

Physicians should advise patients of the reported signs and symptoms of secondary exposure, which may include the following:

- In children: unexpected sexual development including inappropriate enlargement of the penis or clitoris, premature development of pubic hair, increased erections, and aggressive behavior
- In women: changes in hair distribution, increase in acne, or other signs of testosterone effects
- The possibility of secondary exposure to testosterone gel should be brought to the attention of a healthcare provider
- AndroGel 1% should be promptly discontinued until the cause of virilization is identified

Strict adherence to the following precautions is advised to minimize the potential for secondary exposure to testosterone from testosterone gel in men [see Medication Guide]:

- Children and women should avoid contact with unwashed or unclothed application site(s) of men using testosterone gel
- Patients using AndroGel 1% should apply the product as directed and strictly adhere to the following:
  ○ Wash hands with soap and water immediately after application
  ○ Cover the application site(s) with clothing after the gel has dried
  ○ Wash the application site(s) thoroughly with soap and water prior to any situation where skin-to-skin contact of the application site with another person is anticipated
  ○ In the event that unwashed or unclothed skin to which AndroGel 1% has been applied comes in contact with the skin of another person, the general area of contact on the other person should be washed with soap and water as soon as possible [see Dosage and Administration (2.2), Warnings and Precautions (5.1) and Clinical Pharmacology (12.3)].

17.3 Potential for Venous Thromboembolism

Inform patients that AndroGel 1% can cause venous thromboembolism. Advise patients of the signs and symptoms of venous thromboembolism, which may include the following: lower limb pain, edema, or erythema; and dyspnea or chest pain. Advise patients to promptly report the signs and symptoms of venous thromboembolism, discontinue use of AndroGel 1%, and seek urgent medical care.

17.4 Potential for Increase in Blood Pressure

Inform patients that AndroGel 1% can increase BP which can increase cardiovascular risk over time. Instruct patients about the importance of monitoring BP periodically while on Androgel 1%. If BP increases while on AndroGel 1%, antihypertensive medications may need to be started, added, or adjusted to control BP, or AndroGel 1% may need to be discontinued.

17.5 Potential Adverse Reactions with Androgens

Patients should be informed that treatment with androgens may lead to adverse reactions which include:

- Changes in urinary habits such as increased urination at night, trouble starting your urine stream, passing urine many times during the day, having an urge that you have to go to the bathroom right away, having a urine accident, being unable to pass urine and weak urine flow.
- Breathing disturbances, including those associated with sleep, or excessive daytime sleepiness.
- Too frequent or persistent erections of the penis.
- Nausea, vomiting, changes in skin color, or ankle swelling.

17.6 Patients Should Be Advised of the Following Instructions for Use

- Read the Medication Guide before starting AndroGel 1% therapy and to reread it each time the prescription is renewed
- AndroGel 1% should be applied and used appropriately to maximize the benefits and to minimize the risk of secondary exposure in children and women
- Keep AndroGel 1% out of the reach of children
- AndroGel 1% is an alcohol based product and is flammable; therefore avoid fire, flame or smoking until the gel has dried
- It is important to adhere to all recommended monitoring
- Report any changes in their state of health, such as changes in urinary habits, breathing, sleep, and mood
- AndroGel 1% is prescribed to meet the patient's specific needs; therefore, the patient should never share AndroGel 1% with anyone.
- Wait 5 hours before swimming or washing following application of AndroGel 1%. This will ensure that the greatest amount of AndroGel 1% is absorbed into their system.

Marketed by:

ASCEND Therapeutics US, LLC Bridgewater, NJ08807, USA

© 2025 ASCEND Therapeutics US, LLC

2025AG0002 Revised July, 2025

MEDICATION GUIDE
ANDROGEL® (AN DROW JEL) CIII
(testosterone gel) 1% for topical use

What is the most important information I should know about ANDROGEL 1%?
1. ANDROGEL 1% can transfer from your body to others including, children and women. Children and women should avoid contact with the unwashed or not covered (unclothed) areas where ANDROGEL 1% has been applied to your skin. Early signs and symptoms of puberty have occurred in young children who have come in direct contact with testosterone by touching areas where men have used ANDROGEL 1%.
Children
Signs and symptoms of early puberty in a child when they come in direct contact with ANDROGEL 1% may include:
Abnormal sexual changes:

- enlarged penis or clitoris.
- early growth of hair near the vagina or around the penis (pubic hair).
- erections or acting out sexual urges (sex drive).

Behavior problems:

- acting aggressively, behaving in an angry or violent way.

Women
Signs and symptoms in women when they come in direct contact with ANDROGEL 1% may include:

- changes in body hair.
- an abnormal increase in pimples (acne).

Stop using ANDROGEL 1% and call your healthcare provider right away if you see any signs and symptoms in a child or a woman that may have happened through accidental touching of the area where you have applied ANDROGEL 1%.
2. To lower the risk of transfer of ANDROGEL 1% from your body to others, follow these important instructions:

- Apply ANDROGEL 1% only to areas of your shoulders, upper arms, or stomach area (abdomen) that will be covered by a short sleeve t-shirt.
- Wash your hands right away with soap and water after applying ANDROGEL 1%.
- After the gel has dried, cover the application area with clothing. Keep the area covered until you have washed the gel off the application area well or have showered.
- If you expect to have skin-to-skin contact with another person, first wash the application area well with soap and water.
- If a child or woman touches the area where you have applied ANDROGEL 1%, that area on the child or woman should be washed well with soap and water right away.

What is ANDROGEL 1%?
ANDROGEL 1% is a prescription medicine that contains testosterone. ANDROGEL 1% is used to treat adult males who have low or no testosterone due to certain medical conditions.

- Your healthcare provider will test your blood before you start and while you are using ANDROGEL 1%.
- It is not known if ANDROGEL 1% is safe or effective to treat men who have low testosterone due to aging.
- It is not known if ANDROGEL 1% is safe or effective in children younger than 18 years old. Improper use of ANDROGEL 1% may affect bone growth in children.

ANDROGEL 1% is a controlled substance (CIII) because it contains testosterone that can be a target for people who abuse prescription medicines. Keep your ANDROGEL 1% in a safe place to protect it. Never give your ANDROGEL 1% to anyone else, even if they have the same symptoms you have. Selling or giving away this medicine may harm others and is against the law.
ANDROGEL 1% is not meant for use in women.

Do not use ANDROGEL 1% if you:

- have breast cancer.
- have or might have prostate cancer.
- are pregnant. ANDROGEL 1% may harm your unborn baby.
- Women who are pregnant should avoid contact with the area of skin where ANDROGEL 1% has been applied.

Before using ANDROGEL 1%, tell your healthcare provider about all of your medical conditions, including if you:

- have breast cancer.
- have or might have prostate cancer.
- have urinary problems due to an enlarged prostate.
- have heart problems.
- Have high blood pressure or are being treated for high blood pressure.
- have liver or kidney problems.
- have problems breathing while you sleep (sleep apnea).

Tell your healthcare provider about all the medicines you take, including prescription and over-the-counter medicines, vitamins, and herbal supplements. Using ANDROGEL 1% with certain other medicines can affect each other.
Especially, tell your healthcare provider if you take:

- insulin
- corticosteroids
- medicines that decrease blood clotting (blood thinners)

How should I use ANDROGEL 1%?

- See the detailed Instructions for Use for information about how to use ANDROGEL 1% at the end of this Medication Guide.
- It is important that you apply ANDROGEL 1% exactly as your healthcare provider tells you to.
- Your healthcare provider may change your ANDROGEL 1% dose. Do not change your ANDROGEL 1% dose without talking to your healthcare provider.
- Apply ANDROGEL 1% at the same time each morning. ANDROGEL 1% should be applied after showering or bathing.

What are the possible side effects of ANDROGEL 1%?
ANDROGEL 1% can cause serious side effects including:
See “What is the most important information I should know about ANDROGEL 1%?”

- If you already have an enlarged prostate, your symptoms can get worse while using ANDROGEL 1%. This can include:
  ○ increased urination at night.
  ○ trouble starting your urine stream.
  ○ having to pass urine many times during the day.
  ○ having an urge to go to the bathroom right away.
  ○ having a urine accident.
  ○ being unable to pass urine or weak urine flow.
- Possible increased risk of prostate cancer. Your healthcare provider should check you for prostate cancer or any other prostate problems before you start and while you use ANDROGEL 1%.
- Blood clots in the legs or lungs. Signs and symptoms of a blood clot in your leg can include leg pain, swelling, or redness. Signs and symptoms of a blood clot in your lungs can include difficulty breathing or chest pain.
- Increase in blood pressure. AndroGel 1% can increase your blood pressure. Increases in blood pressure can increase the risk of heart attack or stroke over time. If your blood pressure increases while on AndroGel 1%, blood pressure medicines may need to be started. If you are taking blood pressure medicines, new blood pressure medicines may need to be added or your current blood pressure medicines may need to be adjusted to control your blood pressure. If your blood pressure cannot be controlled, AndroGel 1% may need to be stopped. Your healthcare provider will monitor your blood pressure while you are being treated with AndroGel 1%.
- In large doses ANDROGEL 1% may lower your sperm count.
- Swelling of your ankles, feet, or body, with or without heart failure.
- Enlarged or painful breasts.
- Have problems breathing while you sleep (sleep apnea).

Call your healthcare provider right away if you have any of the serious side effects listed above.
The most common side effects of ANDROGEL 1% include:

- acne
- skin irritation where ANDROGEL 1% is applied
- lab test changes
- increased prostate specific antigen (a test used to screen for prostate cancer).

Other side effects include more erections than are normal for you or erections that last a long time.
Tell your healthcare provider if you have any side effect that bothers you or that does not go away.
These are not all the possible side effects of ANDROGEL 1%. For more information, ask your healthcare provider or pharmacist.
Call your doctor for medical advice about side effects. You may report side effects to FDA at 1-800-FDA-1088.

General information about the safe and effective use of ANDROGEL 1%
Medicines are sometimes prescribed for purposes other than those listed in a Medication Guide. Do not use ANDROGEL 1% for a condition for which it was not prescribed. Do not give ANDROGEL 1% to other people, even if they have the same symptoms you have. It may harm them.
It may harm them. You can ask your pharmacist or healthcare provider for information about ANDROGEL 1% that is written for health professionals.

What are the ingredients in ANDROGEL 1%?
Active ingredient: testosterone
Inactive ingredients: carbomer 980, ethyl alcohol 67.0%, isopropyl myristate, purified water and sodium hydroxide.
Marketed by: ASCEND Therapeutics US, LLC, Bridgewater, NJ 08807, USA
© 2025 ASCEND Therapeutics US, LLC
For more information, go to www.ANDROGEL.com or call 1-877-204-1013.

This Medication Guide has been approved by the U.S. Food and Drug Administration Revised: 07/2025

2025AG0002

PATIENT INFORMATION

INSTRUCTIONS FOR USE
ANDROGEL® (AN DROW JEL) CIII
(testosterone gel) 1%
1% for topical use

Read this Instructions for Use for ANDROGEL 1% before you start using it and each time you get a refill. There may be new information. This leaflet does not take the place of talking to your healthcare provider about your medical condition or treatment.

Applying ANDROGEL 1%:

- Before applying ANDROGEL 1%, make sure that your shoulders, upper arms or stomach are clean, dry, and there is no broken skin.
- The application sites for ANDROGEL 1% are the shoulders, upper arms or stomach area (abdomen) that will be covered by a short sleeve t-shirt (see Figure A). Do not apply ANDROGEL 1% to any other parts of your body such as your penis, scrotum, chest, armpits (axillae), knees, or back.

ANDROGEL 1% comes in a pump or in packets.

If you are using the ANDROGEL 1% pump:

- Before using a new bottle of ANDROGEL 1% for the first time, you will need to prime the pump. To prime the ANDROGEL 1% pump, slowly push the pump all the way down 3 times. Do not use any ANDROGEL 1% that came out while priming. Wash it down the sink to avoid accidental exposure to others. Your ANDROGEL 1% pump is ready to use.
- Remove the cap from the pump. Then, position the nozzle over the palm of your hand and slowly push the pump all the way down. Apply ANDROGEL 1% to the application site. You may also apply ANDROGEL 1% directly to the application site.
- Wash your hands with soap and water right away.
- Your healthcare provider will tell you the number of times to press the pump for each dose.

If you are using the ANDROGEL 1% packets:

- Tear open the packet completely at the dotted line. Squeeze from the bottom of the packet to the top.
- Squeeze all of the ANDROGEL 1% out of the packet into the palm of your hand.
- Apply ANDROGEL 1% to the application site. You may also apply ANDROGEL 1% from the packet directly to the application site.
- Let the application areas dry completely before putting on a t-shirt.
- ANDROGEL 1% is flammable until dry. Let ANDROGEL 1% dry before smoking or going near an open flame.
- Wash your hands with soap and water right away after applying ANDROGEL 1%.
- Avoid showering, swimming, or bathing for at least 5 hours after you apply ANDROGEL 1%.

How should I store ANDROGEL 1%?

- Store ANDROGEL 1% at room temperature between 68ºF to 77ºF (20ºC to 25ºC).
- Safely throw away used ANDROGEL 1% in the household trash. Be careful to prevent accidental exposure of children or pets.
- Keep ANDROGEL 1% away from fire.

Keep ANDROGEL 1% and all medicines out of the reach of children.

This Instructions for Use has been approved by the U.S. Food and Drug Administration. Revised: 10/2025

2025AG0002

--- Principal Display Panel 17139-525-30 ---

NDC 17139–525–30 For Topical Use Only
Contains 25 mg of testosterone
(2.5 Grams of gel)

AndroGel® (testosterone gel) 1% CIII

Please read Medication Guide

Rx Only

Topical testosterone products may have different doses, strengths, or application instructions that may result in different systemic exposure.

WARNINGS: Keep out of reach of children. ALCOHOL BASED GELS ARE FLAMMABLE. AVOID FIRE, FLAME OR SMOKING UNTIL GEL HAS DRIED

Ascend Therapeutics

--- Principal Display Panel 17139-550-30 ---

NDC 17139–550–30 For Topical Use Only
Contains 50 mg of testosterone
(5 Grams of gel)

AndroGel® (testosterone gel) 1% CIII

Please read Medication Guide

Rx Only

Topical testosterone products may have different doses, strengths, or application instructions that may result in different systemic exposure.

WARNINGS: Keep out of reach of children. ALCOHOL BASED GELS ARE FLAMMABLE. AVOID FIRE, FLAME OR SMOKING UNTIL GEL HAS DRIED

Ascend Therapeutics

--- Principal Display Panel ---

NDC 17139–501–02

AndroGel® (testosterone gel) 1% CIII

Ascend Therapeutics